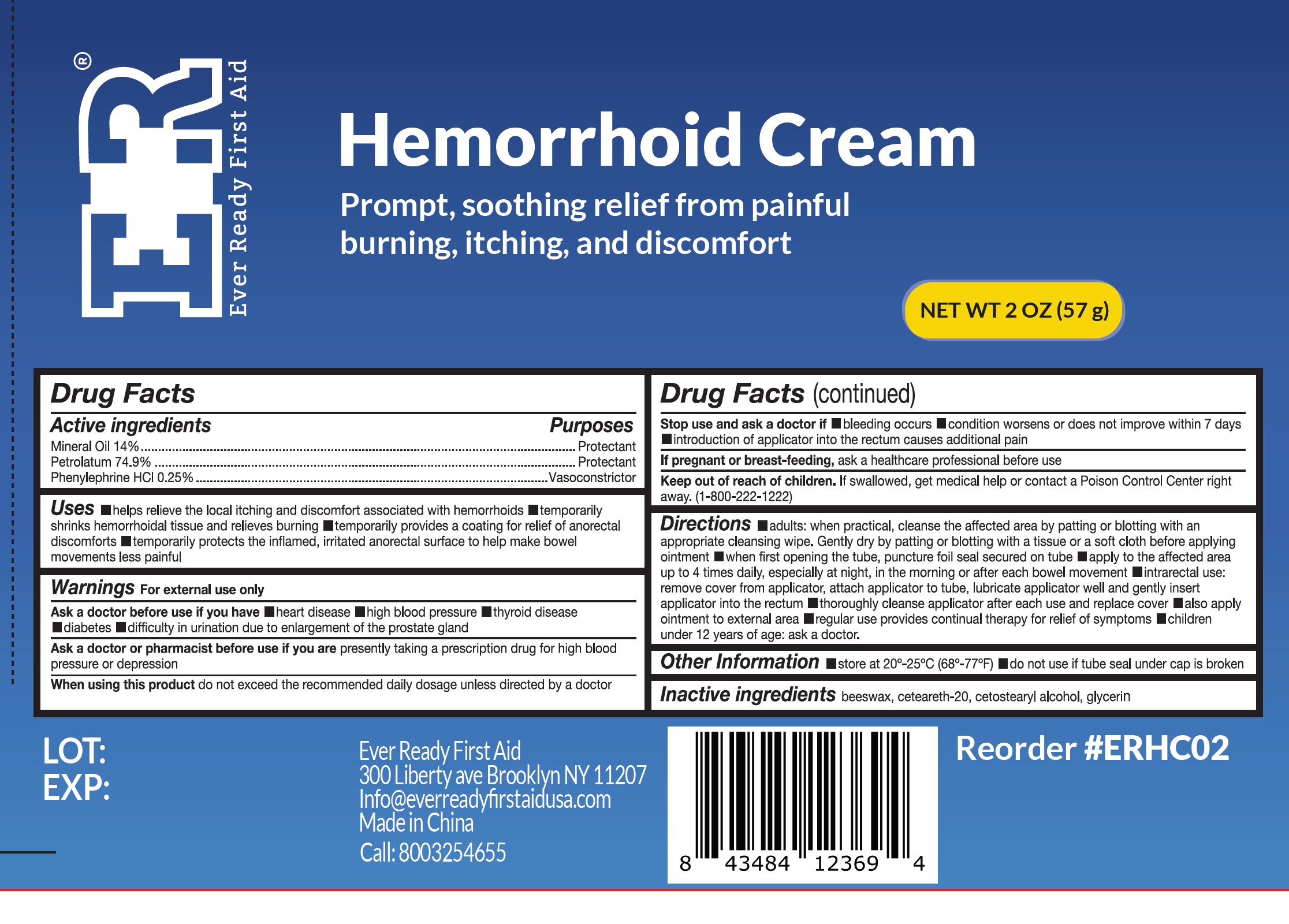 DRUG LABEL: ER Hemorrhoid
NDC: 72976-018 | Form: CREAM
Manufacturer: EVER READY FIRST AID
Category: otc | Type: HUMAN OTC DRUG LABEL
Date: 20240202

ACTIVE INGREDIENTS: MINERAL OIL 0.14 g/1 g; PETROLATUM 0.749 g/1 g; PHENYLEPHRINE HYDROCHLORIDE 0.0025 g/1 g
INACTIVE INGREDIENTS: CETOSTEARYL ALCOHOL; GLYCERIN

72976-018-01 ER hemorrhoids cream

Active Ingredients

Mineral Oil 14%
Petrolatum 74.9%
Phenylephrine HCI 0.25%

Purpose

Protectant
Protectant
Vasoconstrictor

Uses

- helps relieve the local itching and discomfort associated with hemorrhoids
- temporarily shrinks hemorrhoidal tissue and relieves burning
- temporarily provides a coating for relief of anorectal discomforts
- temporarily protects the inflamed, irritated anorectal surface to help make bowel movements less painful

Warnings

For external use only.

Ask a doctor before use if you have

- heart disease
- high blood pressure
- thyroid disease
- diabetes
- difficulty in urination due to enlargement of the prostate gland

Ask a doctor or pharmacist before useif you are presently taking a prescription drug for high blood pressure or depression

WHEN USING

When using this productdo not exceed the recommended daily dosage unless directed by a doctor

Stop use and ask a doctor if

- bleeding occurs
- condition worsens or does not improve within 7 days
- introduction of applicator into the rectum causes additional pain

PREGNANCY OR BREAST FEEDING

If pregnant or breast-feeding, ask a healthcare professional before use

Keep out of reach of children

If swallowed, get medical help or contact a Poison Control Center right away. (1-800-222-1222)

Directions

- adults: when practical, cleanse the affected area by patting or blotting with an appropriate cleansing wipe. Gently dry by patting or blotting with a tissue or a soft cloth before applying ointment
- when first opening the tube, puncture foil seal secured on tube
- apply to the affected area up to 4 times daily, especially at night, in the morning or after each bowel movement
- intrarectal use:remove cover from applicator, attach applicator to tube, lubricate applicator well and gently insert applicator into the rectum
- thoroughly cleanse applicator after each use and replace cover also apply ointment to external area regular use provides continual therapy for relief of symptoms
- children under 12 years of age: ask a doctor

Other Information

- store at 20°-25°C (68°-77°F)
- do not use if tube seal under cap is broken

Inactive Ingredients

beeswax, ceteareth-20, cetostearyl alcohol, glycerin